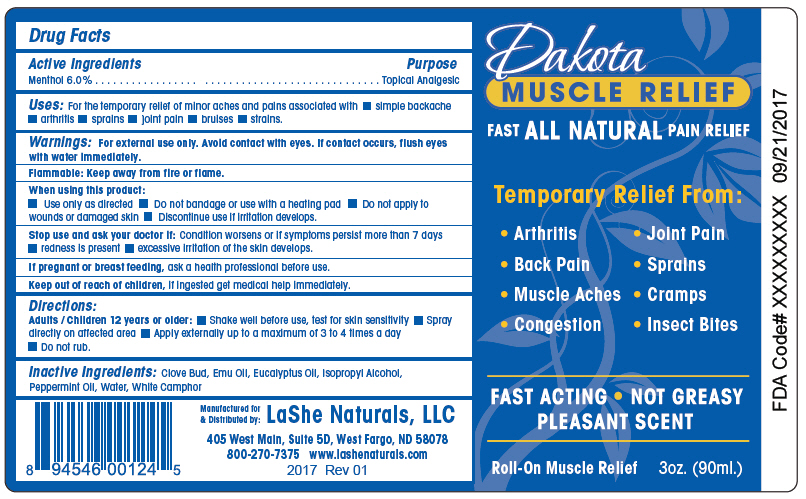 DRUG LABEL: Dakota Muscle Relief Roll-On
NDC: 71680-002 | Form: SOLUTION
Manufacturer: LaShe Naturals, LLC
Category: otc | Type: HUMAN OTC DRUG LABEL
Date: 20211208

ACTIVE INGREDIENTS: MENTHOL, UNSPECIFIED FORM 60 mg/1 mL
INACTIVE INGREDIENTS: ISOPROPYL ALCOHOL; Water; Peppermint Oil; Eucalyptus Oil; Camphor Oil, White; CLOVE OIL; Emu Oil; Xanthan Gum

Dakota Muscle Relief Roll-On

Drug Facts

Active Ingredients

Menthol 6.0%

Purpose

Topical Analgesic

Uses

For the temporary relief of minor aches and pains associated with

- simple backache
- arthritis
- sprains
- joint pain
- bruises
- strains.

Warnings

For external use only. Avoid contact with eyes. If contact occurs, flush eyes with water immediately.

Flammable

Keep away from fire or flame.

When using this product:

- Use only as directed
- Do not bandage or use with a heating pad
- Do not apply to wounds or damaged skin
- Discontinue use if irritation develops.

Stop use and ask your doctor if:

Condition worsens or if symptoms persist more than 7 days

- redness is present
- excessive irritation of the skin develops.

PREGNANCY OR BREAST FEEDING

If pregnant or breast feeding, ask a health professional before use.

Keep out of reach of children, if ingested get medical help immediately.

Directions

Adults / Children 12 years or older:

- Shake well before use, test for skin sensitivity
- Spray directly on affected area
- Apply externally up to a maximum of 3 to 4 times a day
- Do not rub.

Inactive Ingredients

Clove Bud, Emu Oil, Eucalyptus Oil, Isopropyl Alcohol, Peppermint Oil, Water, White Camphor

Distributed by:
LaShe Naturals, LLC
405 West Main, Suite 5D, West Fargo, ND 58078

PRINCIPAL DISPLAY PANEL - 90 ml Bottle Label

Dakota
MUSCLE RELIEF

FAST ALL NATURAL PAIN RELIEF

Temporary Relief From:

- Arthritis
- Joint Pain
- Back Pain
- Sprains
- Muscle Aches
- Cramps
- Congestion
- Insect Bites

FAST ACTING • NOT GREASY
PLEASANT SCENT

Roll-On Muscle Relief
3oz. (90ml.)